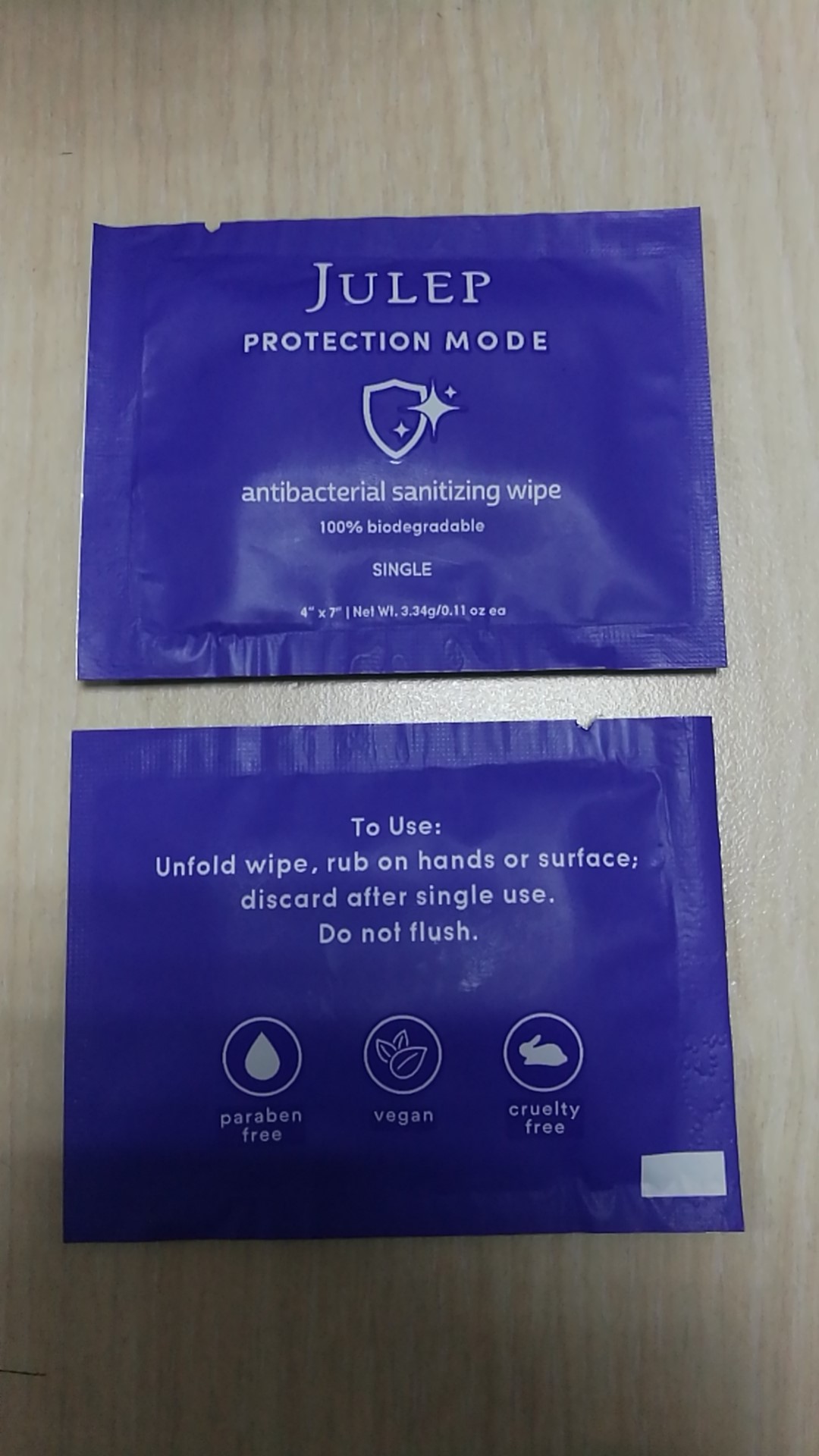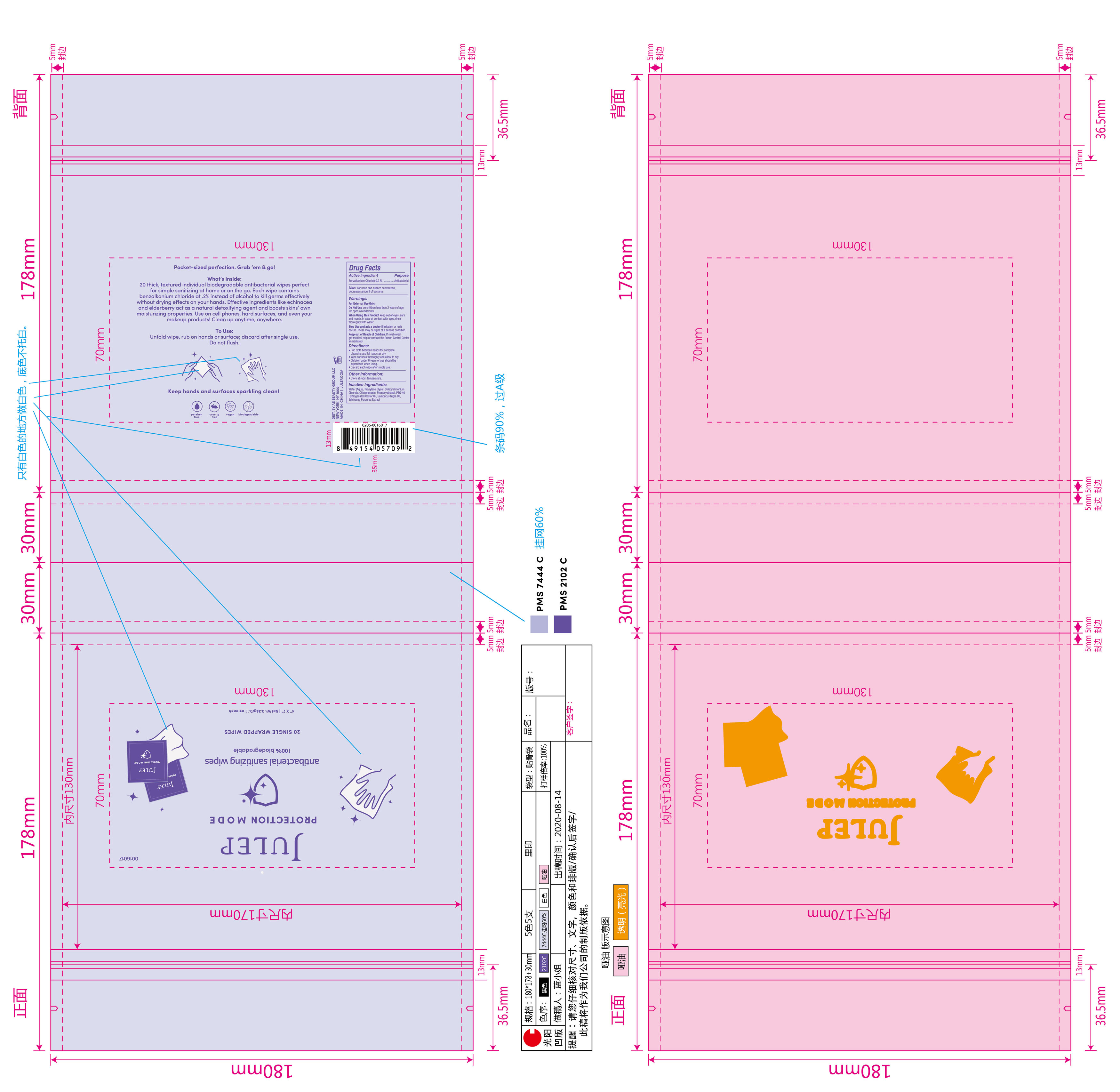 DRUG LABEL: JULEP antibacterial sanitizing wipe
NDC: 76635-121 | Form: CLOTH
Manufacturer: Hangzhou Glamcos Biotech CO.,LTD
Category: otc | Type: HUMAN OTC DRUG LABEL
Date: 20231123

ACTIVE INGREDIENTS: BENZALKONIUM CHLORIDE 0.2 g/100 g
INACTIVE INGREDIENTS: POLYOXYL 40 HYDROGENATED CASTOR OIL; PROPYLENE GLYCOL; CHLORPHENESIN; PHENOXYETHANOL; WATER; DIDECYLDIMONIUM CHLORIDE; ECHINACEA PURPUREA; SAMBUCUS NIGRA SEED OIL

Active Ingredient

Benzalkonium Chloride 0.2%

Purpose

Antibacterial

Use

For hand and surface sanitization, decrease amount of bacteria.

Warnings

For External Use Only.
Do Not Use on children less than 2 years of age.
On open wounds/cuts.
When Using This Product keep out of eyes,ears and mouth.In case of contact with eyes,rinse thoroughly with water.
Stop use and ask a doctor if irritation or rash occurs.These may be signs of a serious condition.

On Children

Keep out of reach of children. If swallowed,get medical help or contact the poison control center immediately.

Directions

Rub cloth between hands for complete cleansing and let hands air dry.
Wipe surface thoroughly and alow to dry.
Children under 6 years of age should be supervised when using.
Discard each wipe after single use.

Inactive ingredients

Water(Aqua)，Propylene Glycol，DidecyldimoniumChloride , Chlorphenesin， Phenoxyethanol，PEG-40 Hydrogenated Castor Oil，Sambucus Nigra Oil，Echinacea Purpurea Extract